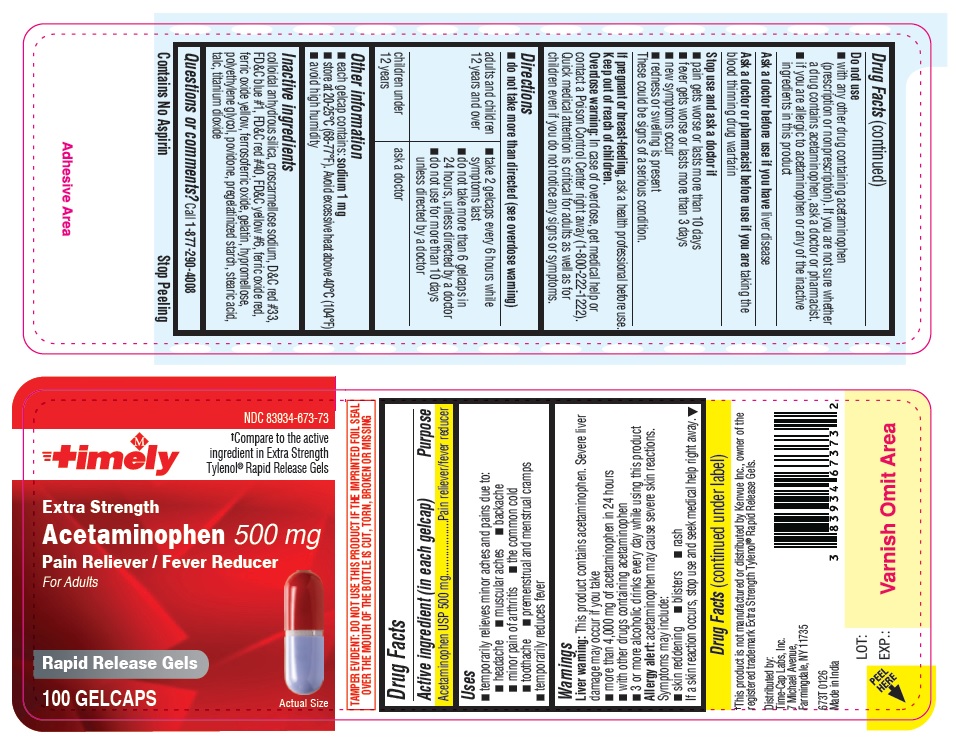 DRUG LABEL: Extra Strength Acetaminophen
NDC: 83934-673 | Form: TABLET
Manufacturer: TIME CAP LABORATORIES, INC.
Category: otc | Type: HUMAN OTC DRUG LABEL
Date: 20260117

ACTIVE INGREDIENTS: ACETAMINOPHEN 500 mg/1 1
INACTIVE INGREDIENTS: TITANIUM DIOXIDE; POVIDONE; FD&C YELLOW NO. 6; FD&C RED NO. 40; FERRIC OXIDE YELLOW; POLYETHYLENE GLYCOL, UNSPECIFIED; STEARIC ACID; TALC; SILICON DIOXIDE; D&C RED NO. 33; FD&C BLUE NO. 1; FERRIC OXIDE RED; FERROSOFERRIC OXIDE; GELATIN; CROSCARMELLOSE SODIUM; STARCH, CORN; HYPROMELLOSE, UNSPECIFIED

673T Timely Extra Strength Acetaminophen Gelcaps

Active ingredient (in each gelcap)

Acetaminophen USP 500 mg

Purpose

Pain reliever/fever reducer

Uses

- temporarily relieves minor aches and pains due to:

- headache

- muscular aches

- backache

- minor pain of arthritis

- the common cold

- toothache

- premenstrual and menstrual cramps

- temporarily reduces fever

Warnings

Liver warning:This product contains acetaminophen. Severe liver damage may occur if you take

- more than 4,000 mg of acetaminophen in 24 hours
- with other drugs containing acetaminophen
- 3 or more alcoholic drinks every day while using this product

Allergy alert:acetaminophen may cause severe skin reactions. Symptoms may include:

- skin reddening
- blisters
- rash

If a skin reaction occurs, stop use and seek medical help right away.

Do not use

- with any other drug containing acetaminophen (prescription or nonprescription). If you are not sure whether a drug contains acetaminophen, ask a doctor or pharmacist.
- if you are allergic to acetaminophen or any of the inactive ingredients in this product

Ask a doctor before use if you have liver disease

Ask a doctor or pharmacist before use if you are taking the blood thinning drug warfarin

Stop use and ask a doctor if

- pain gets worse or lasts more than 10 days
- fever gets worse or lasts more than 3 days
- new symptoms occur
- redness or swelling is present

These could be signs of a serious condition.

PREGNANCY OR BREAST FEEDING

If pregnant or breast-feeding, ask a health professional before use.

Keep out of reach of children.

OVERDOSAGE

Overdose warning: In case of overdose, get medical help or contact a Poison Control Center right away (1-800-222-1222). Quick medical attention is critical for adults as well as for children even if you do not notice any signs or symptoms.

Directions

- do not take more than directed (see overdose warning)

adults and children 12 years and over | - take 2 gelcaps every 6 hours while symptoms last - do not take more than 6 gelcaps in 24 hours, unless directed by a doctor - do not use for more than 10 days unless directed by a doctor
children under 12 years | ask a doctor

Other information

- each gelcap contains: sodium 1 mg
- store between 20-25°C (68-77°F). Avoid excessive heat above 40°C (104°F)
- avoid high humidity

INACTIVE INGREDIENT

Inactive ingredients colloidal anhydrous silica, croscarmellose sodium, D&C red #33, FD&C blue #1, FD&C red #40, FD&C yellow #6, ferric oxide red, ferric oxide yellow, ferrosoferric oxide, gelatin, hypromellose, polyethylene glycol, povidone, pregelatinized starch, stearic acid, talc, titanium dioxide

Questions or comments?Call 1-877-290-4008